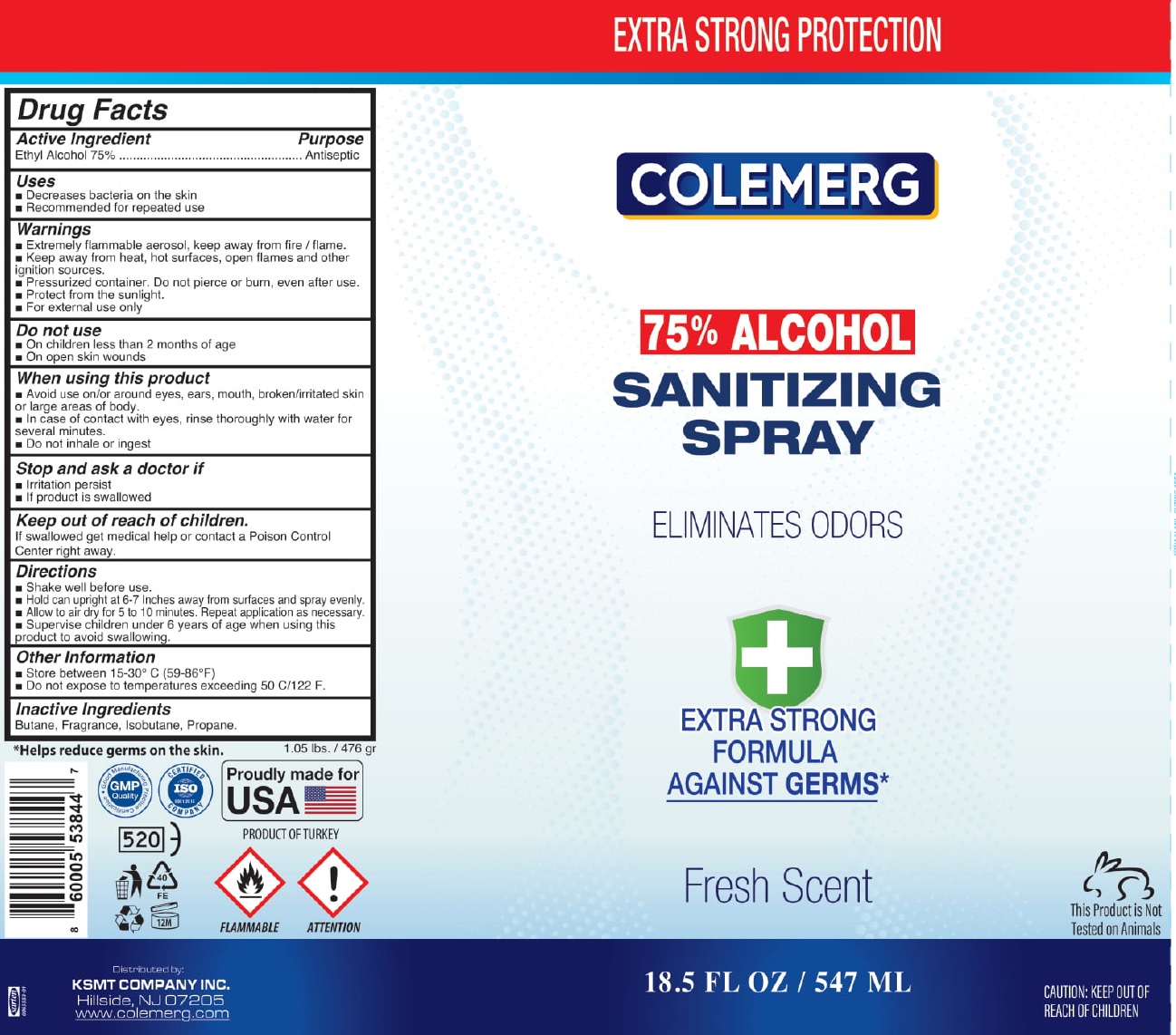 DRUG LABEL: Colemerg 75 Alcohol Sanitizing
NDC: 81547-001 | Form: SPRAY
Manufacturer: KSMT COMPANY INCORPORATED
Category: otc | Type: HUMAN OTC DRUG LABEL
Date: 20210218

ACTIVE INGREDIENTS: ALCOHOL 75 mL/100 mL
INACTIVE INGREDIENTS: BUTANE; ISOBUTANE; PROPANE

Colemerg 75% Alcohol Sanitizing Spray

Active Ingredient

Ethyl Alcohol 75%

Purpose

Antiseptic

Uses

- Decreases bacteria on the skin
- Recommended for repeated use

Warnings

- Extermely flammable aerosol, keep away from fire / flame.
- Keep away from heat, hot surfaces, open flames and other ignition sources.
- Pressurized contiainer, Do not pierce or burn, even after use.
- Protect from the sunlight.
- For external use only

Do not use

- On children less than 2 months of age
- On open skin wounds

When using this product

- Avoid use on/or around eyes, ears, mouth, broken/irritated skin or large areas of body.
- In case of contact with eyes, rinse thoroughly with water for several minutes.
- Do not inhale or ingest

Stop and ask a doctor if

- Irritation persist
- If product is swallowed

Keep out of reach of children.

If swallowed get medical helo or contact a Poison Control Center right away.

Directions

- Shake well before use.
- Hold can upright at 6-7 inches away from surfaces and spray evenly.
- Allow to air dry for 5 to 10 minutes. Repeat application as necessary.
- Supervise children under 6 years of age when using this product to avoid swallowing.

Other Information

- Store between 15-30° C (59-86°F)
- Do not expose to temperature exceeding 50 C/122 F.

Inactive Ingredients

Butane, Fragrance, Isobutane, Propane.